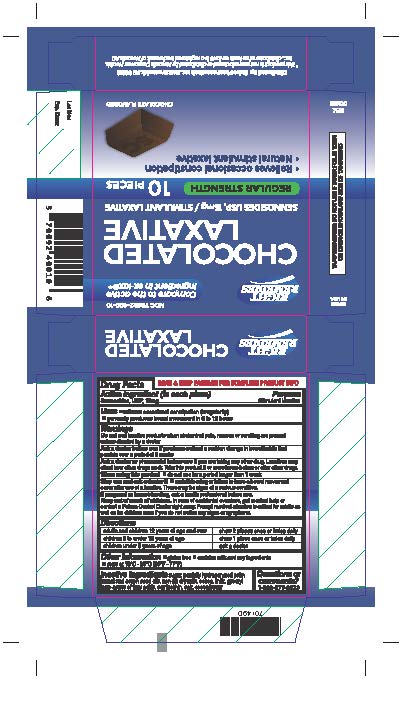 DRUG LABEL: Chocolated Laxative
NDC: 70692-400 | Form: BAR, CHEWABLE
Manufacturer: Strive Pharmaceuticals Inc.
Category: otc | Type: HUMAN OTC DRUG LABEL
Date: 20180301

ACTIVE INGREDIENTS: SENNOSIDES 15 mg/1 1
INACTIVE INGREDIENTS: COW MILK; GLYCERYL LACTOPALMITATE/STEARATE; SODIUM CHLORIDE; SKIM MILK; SUCROSE; HYDROGENATED PALM/PALM KERNEL OIL PEG-6 ESTERS; HYDROGENATED COTTONSEED OIL; COCOA; COCOA BUTTER; LECITHIN, SOYBEAN

CHOCOLATED LAXATIVE
SENNOSIDES USP 15MG

ACTIVE INGREDIENT

Sennosides USP 15mg

INACTIVE INGREDIENT

sugar, partially hydrogenetated palm kernel and cotton seed oils, non-fat dry milk, cocoa, milk, gyceryl lacto esters of fatty acids, soy lecithin, cocoa butter.

DOSAGE AND ADMINISTRATION

adults and children 12 years of age and over | chew 2 pieces once or twice daily
children 6 to under 12 years of age | chew 1 piece once or twice daily
children under 6 years of age | ask a doctor

INDICATIONS AND USAGE

* relieves occasional constipation (irregularity)
* generally produces bowel movement in 6 to 12 hours

Do not use laxative products when abdominal pain, nausea or vomiting are present unless directed by a doctor.

Ask a doctor before use if you have noticed a sudden change in bowel habits that persists over a period of 2 weeks.

Ask a doctor or Pharmacist before use if you are taking any other drug. Laxatives may affect how other drugs work. Take this product 2 or more hours before or after other drugs.

When using this product * do not use for a period longer than 1 week.

Stop use and ask a doctor if * rectal bleeding or failure to have a bowel movement occur after use of a laxative. These may be signs of a serious condition.

If pregnant or breast-feeding,ask a health professional before use.

Keep out of reach of children. In case of accidental overdose, get medical help or contact a Poison Control Center right away. Prompt medical attention is critical for adults as well as for children even if you do not notice any signs or symptoms.

KEEP OUT OF REACH OF CHILDREN

In case of accidental overdose, get medical help or contact a Poison Control Center right away. Prompt medical attention is critical for adults as well as for children even if you do not notice any signs or symptoms.

PURPOSE

Stimulant laxative

OTHER SAFETY INFORMATION

* contains milk and soy ingredients

* gluten free

* store at 15°C - 25°C (59°F-77°F)